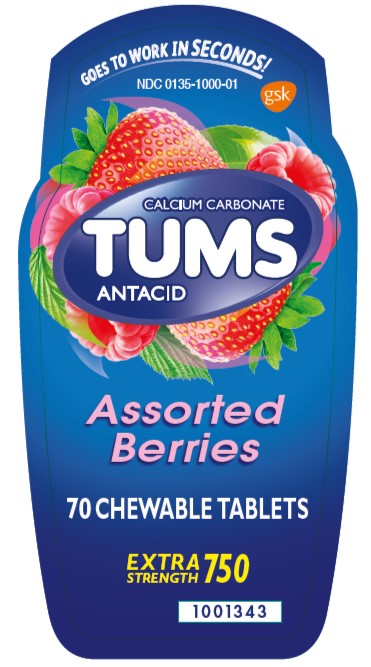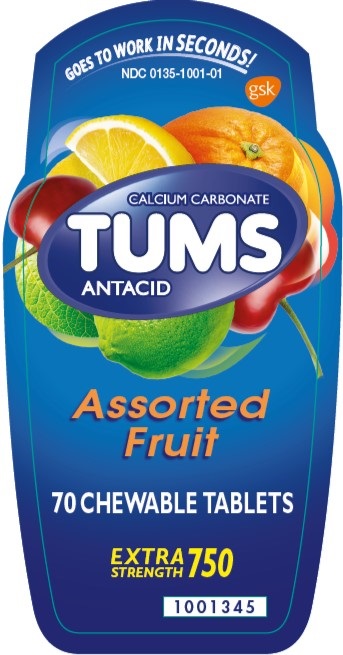 DRUG LABEL: TUMS
NDC: 0135-1000 | Form: TABLET
Manufacturer: Haleon US Holdings LLC
Category: otc | Type: HUMAN OTC DRUG LABEL
Date: 20240303

ACTIVE INGREDIENTS: CALCIUM CARBONATE 750 mg/1 1
INACTIVE INGREDIENTS: ADIPIC ACID; STARCH, CORN; CROSPOVIDONE, UNSPECIFIED; FD&C BLUE NO. 1 ALUMINUM LAKE; ALUMINUM OXIDE; FD&C RED NO. 40; MAGNESIUM STEARATE; MALTODEXTRIN; SUCROSE; TALC

Drug Facts

Active ingredient (in each tablet)

Calcium carbonate 750 mg

Purpose

Antacid

Uses

relieves

- heartburn
- acid indigestion
- sour stomach
- upset stomach associated with these symptoms

Warnings

Ask a doctor or pharmacist before use if you are

presently taking a prescription drug. Antacids may interact with certain prescription drugs.

When using this product

- do not take more than 10 tablets in 24 hours
- if pregnant do not take more than 6 tablets in 24 hours
- do not use the maximum dosage for more than 2 weeks except under the advice and supervision of a doctor

Directions

- adults and children 12 years of age and over:chew 2-4 tablets as symptoms occur, or as directed by a doctor
- do not take for symptoms that persist for more than 2 weeks unless advised by a doctor

Other information

- each tablet contains:elemental calcium 300 mg, magnesium 10 mg
- store below 30oC (86oF)

Inactive ingredients (Assorted Berries)

adipic acid, corn starch, crospovidone, dextrose, FD&C blue 1 lake, FD&C red 40 lake, flavors, magnesium stearate, maltodextrin, sucrose, talc

Inactive ingredient (Assorted Fruit)

adipic acid, corn starch, crospovidone, D&C red 27 lake, D&C red 30 lake, D&C yellow 10 lake, dextrose, FD&C blue 1 lake, FD&C yellow 6 lake, flavors, magnesium stearate, maltodextrin, sucrose, talc

Questions?

1-800-897-7535

Additional Information

DO NOT USE IF PRINTED SEAL UNDER CAP IS TORN OR MISSING.

Dist. by:

GSK Consumer Healthcare

Warren, NJ 07059

©2021 GSK or licensor.

PRINCIPAL DISPLAY PANEL

NDC 0135-1000-01

TUMS

CALCIUM CARBONATE

ANTACID

Assorted Berries

GOES TO WORK IN SECONDS!

70 CHEWABLE TABLETS

EXTRA STRENGTH 750

Front Label: 1001343

Back Label: 1001344

Principal Display Panel

NDC 0135-1001-01

TUMS

CALCIUM CARBONATE

ANTACID

Assorted Fruit

GOES TO WORK IN SECONDS!

70 CHEWABLE TABLETS

EXTRA STRENGTH 750

Front Label: 1001345

Back Label: 1001346